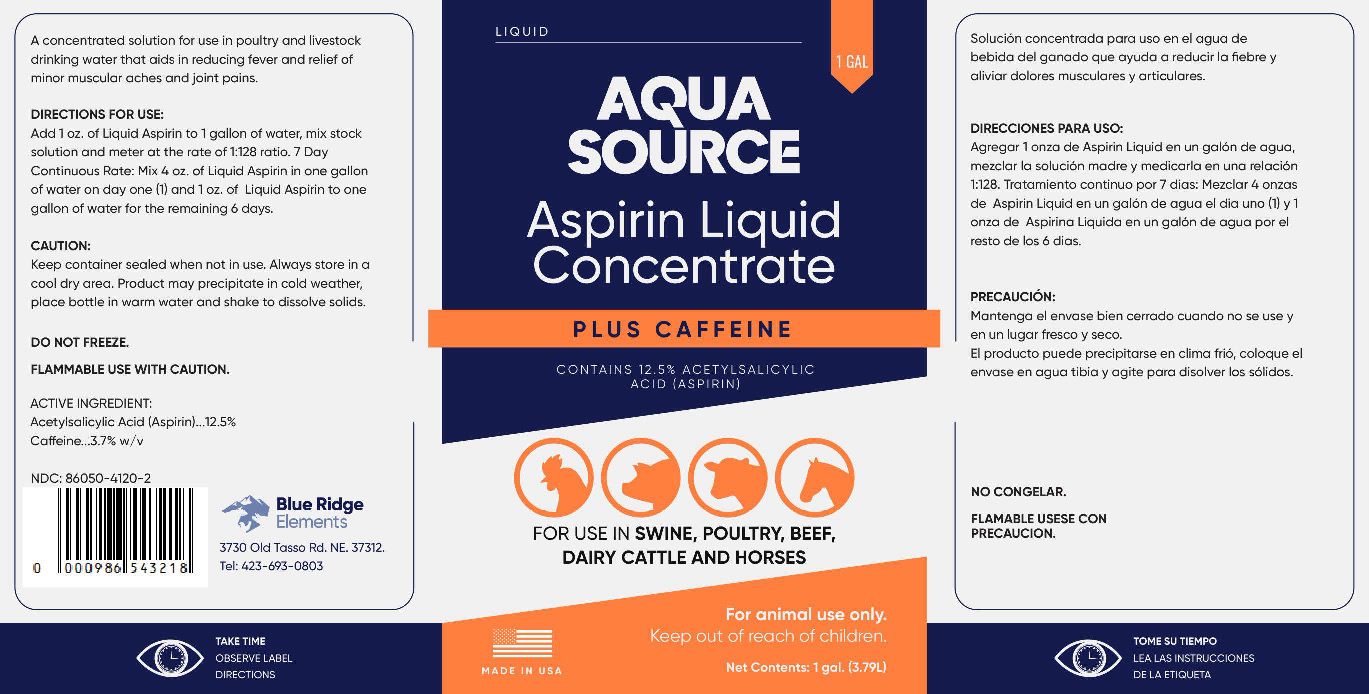 DRUG LABEL: AquaSource Aspirin Liquid Concentrate plus Caffeine
NDC: 86050-4120 | Form: LIQUID
Manufacturer: Blendpack, Inc.
Category: animal | Type: OTC ANIMAL DRUG LABEL
Date: 20230913

ACTIVE INGREDIENTS: ASPIRIN 125 g/1 L; CAFFEINE 37 g/1 L

AquaSource Aspirin Liquid Concentrate plus Caffeine

Product Type:

A Concentrated Aspirin solution for use in Livestock and Poultry Drinking Water

Directions for Use:

Add 1 oz. AquaSource Liquid Aspirin to 1 gallon of water, mix stock solution and meter at the rate of 1:128 ratio.

7 Day Continuous Rate:

Mix 4 oz. of AquaSource Liquid Aspirin in one gallon of water on day one (1) and 1 oz. of AquaSource Liquid Aspirin to one gallon of water for the remaining 6 days.

Caution:

For Animal Use Only

Keep Out of Reach of Children

Keep container sealed when not in use.

Always store in a cool dry area.

Product may precipitate in cold weather, place bottle in warm water and shake to dissolve solids.

DO NOT FREEZE

FLAMMABLE USE WITH CAUTION.

TAKE TIME OBSERVE LABEL DIRECTIONS

PACKAGE LABEL

Add image transcription here...